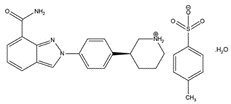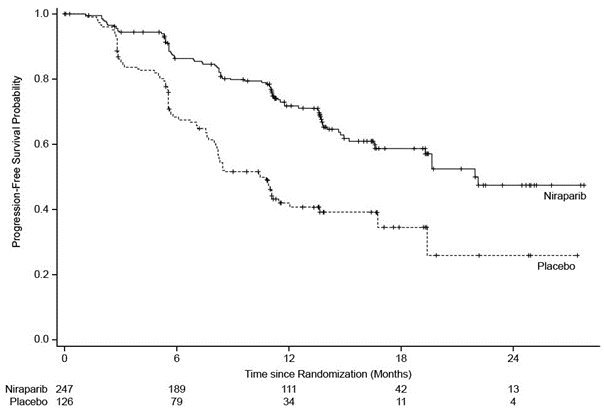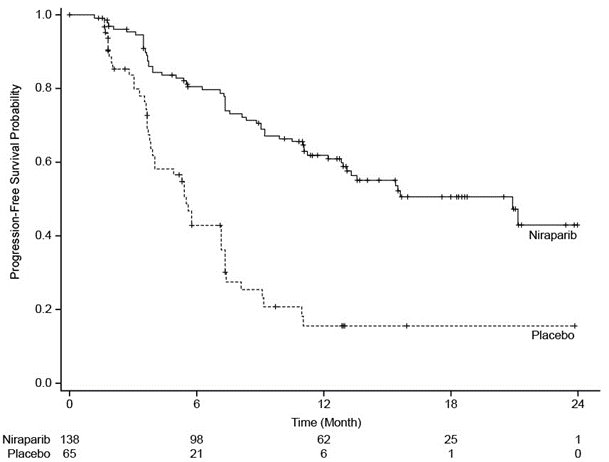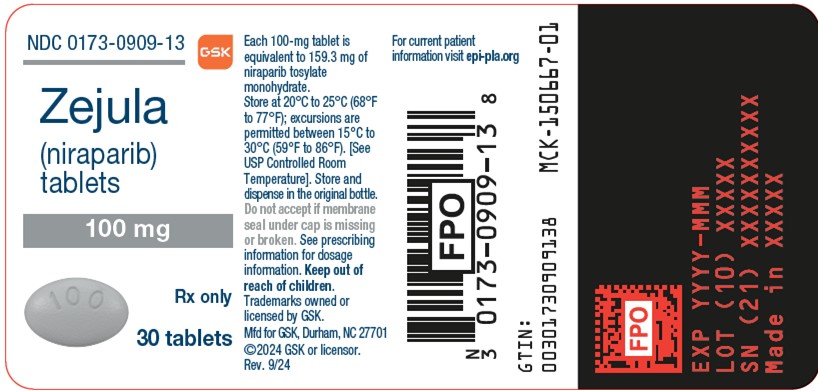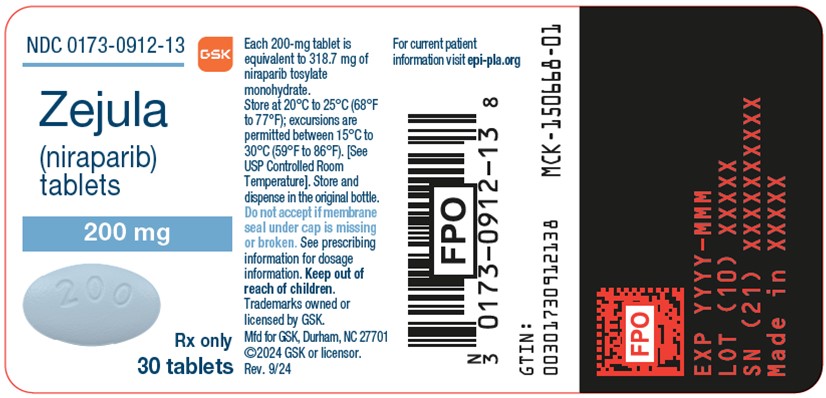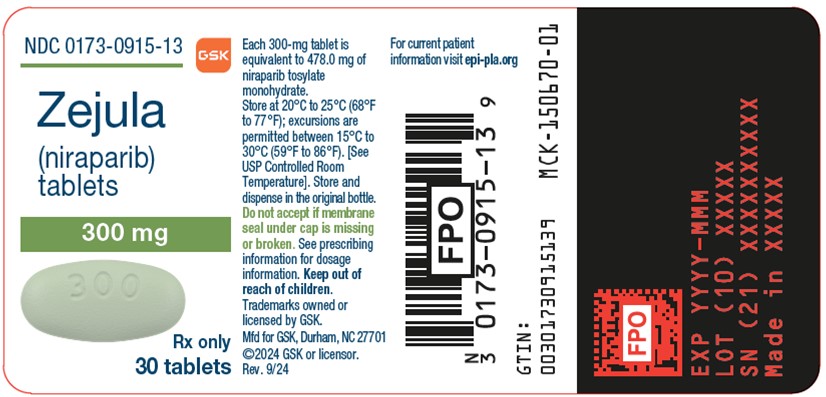 DRUG LABEL: ZEJULA
NDC: 0173-0909 | Form: TABLET, FILM COATED
Manufacturer: GlaxoSmithKline LLC
Category: prescription | Type: HUMAN PRESCRIPTION DRUG LABEL
Date: 20250618

ACTIVE INGREDIENTS: NIRAPARIB TOSYLATE 100 mg/1 1
INACTIVE INGREDIENTS: CROSPOVIDONE, UNSPECIFIED; LACTOSE MONOHYDRATE; MAGNESIUM STEARATE; MICROCRYSTALLINE CELLULOSE; POVIDONE, UNSPECIFIED; SILICON DIOXIDE; WATER

HIGHLIGHTS OF PRESCRIBING INFORMATION

These highlights do not include all the information needed to use ZEJULA safely and effectively. See full prescribing information for ZEJULA.
ZEJULA (niraparib) tablets, for oral use
Initial U.S. Approval: 2017

RECENT MAJOR CHANGES

Indications and Usage (1.1) | 6/2025
Dosage and Administration (2.1) | 6/2025
Warnings and Precautions (5.1) | 6/2025

1 INDICATIONS AND USAGE

ZEJULA is a poly (ADP-ribose) polymerase (PARP) inhibitor indicated:

- for the maintenance treatment of adult patients with advanced epithelial ovarian, fallopian tube, or primary peritoneal cancer who are in a complete or partial response to first-line platinum-based chemotherapy and whose cancer is associated with homologous recombination deficiency (HRD)-positive status defined by either
  - a deleterious or suspected deleterious BRCA mutation, and/or
  - genomic instability. (1.1, 2.1)
- for the maintenance treatment of adult patients with deleterious or suspected deleterious germline BRCA-mutated recurrent epithelial ovarian, fallopian tube, or primary peritoneal cancer who are in a complete or partial response to platinum-based chemotherapy. Select patients for therapy based on an FDA-approved companion diagnostic for ZEJULA. (1.2, 2.1)

2 DOSAGE AND ADMINISTRATION

- First-line maintenance treatment of HRD-positive advanced ovarian cancer:
  - For patients weighing <77 kg (<170 lbs) OR with a platelet count <150,000/mcL, the recommended dosage is 200 mg taken orally once daily. (2.2)
  - For patients weighing ≥77 kg (≥170 lbs) AND a platelet count ≥150,000/mcL, the recommended dosage is 300 mg taken orally once daily. (2.2)
- Maintenance treatment of recurrent germline BRCA-mutated ovarian cancer: The recommended dosage is 300 mg taken orally once daily. (2.2)
- Continue treatment until disease progression or unacceptable toxicity. (2.2)
- ZEJULA may be taken with or without food. (2.2)
- For adverse reactions, consider interruption of treatment, dose reduction, or dose discontinuation. (2.3)
- For patients with moderate hepatic impairment, recommended dosage is 200 mg taken orally once daily. (2.4)

3 DOSAGE FORMS AND STRENGTHS

Tablets: 100 mg, 200 mg, 300 mg. (3)

4 CONTRAINDICATIONS

None. (4)

5 WARNINGS AND PRECAUTIONS

- Myelodysplastic Syndrome/Acute Myeloid Leukemia (MDS/AML): MDS/AML occurred in patients exposed to ZEJULA, and some cases were fatal. Monitor patients for hematological toxicity and discontinue if MDS/AML is confirmed. (5.1)
- Bone Marrow Suppression: Test complete blood counts weekly for the first month, monthly for the next 11 months, and periodically thereafter for clinically significant changes. (5.2)
- Hypertension and Cardiovascular Effects: Monitor blood pressure and heart rate at least weekly for the first 2 months, then monthly for the first year and periodically thereafter during treatment with ZEJULA. Manage with antihypertensive medications and adjustment of the dose of ZEJULA, if necessary. (5.3)
- Posterior Reversible Encephalopathy Syndrome (PRES): PRES has occurred in patients treated with ZEJULA. Discontinue ZEJULA if PRES is confirmed. (5.4)
- Embryo-Fetal Toxicity: ZEJULA can cause fetal harm. Advise females of reproductive potential of the potential risk to a fetus and to use effective contraception. (5.5, 8.1, 8.3)

6 ADVERSE REACTIONS

Most common adverse reactions (incidence ≥10%) in patients who received ZEJULA were nausea, thrombocytopenia, anemia, fatigue, constipation, musculoskeletal pain, abdominal pain, vomiting, neutropenia, decreased appetite, leukopenia, insomnia, headache, dyspnea, rash, diarrhea, hypertension, cough, dizziness, acute kidney injury, urinary tract infection, and hypomagnesemia. (6.1)

To report SUSPECTED ADVERSE REACTIONS, contact GlaxoSmithKline at 1-888-825-5249 or FDA at 1-800-FDA-1088 or www.fda.gov/medwatch.

8 USE IN SPECIFIC POPULATIONS

Lactation: Advise not to breastfeed. (8.2)

FULL PRESCRIBING INFORMATION

1 INDICATIONS AND USAGE

1.1 First-Line Maintenance Treatment of HRD-Positive Advanced Ovarian Cancer

ZEJULA is indicated for the maintenance treatment of adult patients with advanced epithelial ovarian, fallopian tube, or primary peritoneal cancer who are in a complete or partial response to first-line platinum-based chemotherapy and whose cancer is associated with homologous recombination deficiency (HRD)-positive status defined by either:

- a deleterious or suspected deleterious BRCA mutation, and/or
- genomic instability.

1.2 Maintenance Treatment of Recurrent Germline BRCA-Mutated Ovarian Cancer

ZEJULA is indicated for the maintenance treatment of adult patients with deleterious or suspected deleterious germline BRCA-mutated (gBRCAmut) recurrent epithelial ovarian, fallopian tube, or primary peritoneal cancer who are in a complete or partial response to platinum-based chemotherapy.

Select patients for therapy based on an FDA-approved companion diagnostic for ZEJULA [see Dosage and Administration (2.1)].

2 DOSAGE AND ADMINISTRATION

2.1 Patient Selection

First-Line Maintenance Treatment of HRD-Positive Advanced Ovarian Cancer

Select patients for first-line maintenance treatment of advanced ovarian cancer with ZEJULA based on the presence of HRD defined by either a deleterious or suspected deleterious BRCA mutation, and/or genomic instability [see Clinical Studies (14.1)].

An FDA-approved test for detection of HRD-positive status for selecting patients for treatment with ZEJULA is not currently available.

Maintenance Treatment of Recurrent Germline BRCA-Mutated Ovarian Cancer

Select patients for the maintenance treatment of recurrent ovarian cancer with ZEJULA based on the presence of deleterious or suspected deleterious germline BRCA mutations [see Clinical Studies (14.2)].

Information on FDA-approved tests for the detection of deleterious or suspected deleterious germline BRCA mutations for this indication is available at https://www.fda.gov/companiondiagnostics.

2.2 Recommended Dosage and Administration

Continue treatment with ZEJULA until disease progression or unacceptable toxicity.

Instruct patients to take their dose of ZEJULA at approximately the same time each day. Advise patients to swallow tablets whole and not to chew, crush, or split ZEJULA prior to swallowing. ZEJULA may be taken with or without food. Bedtime administration may be a potential method for managing nausea.

In the case of a missed dose of ZEJULA, instruct patients to take their next dose at its regularly scheduled time. If a patient vomits or misses a dose of ZEJULA, an additional dose should not be taken.

First-Line Maintenance Treatment of HRD-Positive Advanced Ovarian Cancer

- For patients weighing <77 kg (<170 lbs) OR with a platelet count of <150,000/mcL, the recommended dosage is 200 mg taken orally once daily.
- For patients weighing ≥77 kg (≥170 lbs) AND who have a platelet count ≥150,000/mcL, the recommended dosage is 300 mg taken orally once daily.

For the maintenance treatment of advanced ovarian cancer, start ZEJULA no later than 12 weeks after their most recent platinum-containing regimen.

Maintenance Treatment of Recurrent Germline BRCA-Mutated Ovarian Cancer

The recommended dosage of ZEJULA is 300 mg taken orally once daily.

For the maintenance treatment of recurrent ovarian cancer, start ZEJULA no later than 8 weeks after their most recent platinum-containing regimen.

2.3 Dosage Modifications for Adverse Reactions

To manage adverse reactions, consider interruption of treatment, dose reduction, or dose discontinuation. The recommended dosage modifications for adverse reactions are listed in Tables 1, 2, and 3.

Table 1. Recommended Dosage Modifications for Adverse Reactions
Starting Dose Level | 200 mg | 300 mg
First dose reduction | 100 mg/daya | 200 mg/day
Second dose reduction | Discontinue ZEJULA. | 100 mg/daya
a If further dose reduction below 100 mg/day is required, discontinue ZEJULA.

Table 2. Dosage Modifications for Non-Hematologic Adverse Reactions
Non-hematologic CTCAE ≥Grade 3 adverse reaction that persists despite medical management | - Withhold ZEJULA for a maximum of 28 days or until resolution of adverse reaction. - Resume ZEJULA at a reduced dose per Table 1.
CTCAE ≥Grade 3 treatment-related adverse reaction lasting more than 28 days while patient is administered ZEJULA 100 mg/day | Discontinue ZEJULA.
CTCAE = Common Terminology Criteria for Adverse Events.

Table 3. Dosage Modifications for Hematologic Adverse Reactions
Monitor complete blood counts weekly for the first month, monthly for the next 11 months of treatment, and periodically after this time [see Warnings and Precautions (5.2)].
Platelet count <100,000/mcL | First occurrence:; - Withhold ZEJULA for a maximum of 28 days and monitor blood counts weekly until platelet counts return to ≥100,000/mcL. - Resume ZEJULA at same or reduced dose per Table 1. - If platelet count is <75,000/mcL, resume at a reduced dose.; Second occurrence:; - Withhold ZEJULA for a maximum of 28 days and monitor blood counts weekly until platelet counts return to ≥100,000/mcL. - Resume ZEJULA at a reduced dose per Table 1. - Discontinue ZEJULA if the platelet count has not returned to acceptable levels within 28 days of the dose interruption period or if the patient has already undergone dose reduction to 100 mg once daily.a
Neutrophil <1,000/mcL or hemoglobin <8 g/dL | - Withhold ZEJULA for a maximum of 28 days and monitor blood counts weekly until neutrophil counts return to ≥1,500/mcL or hemoglobin returns to ≥9 g/dL. - Resume ZEJULA at a reduced dose per Table 1. - Discontinue ZEJULA if neutrophils and/or hemoglobin have not returned to acceptable levels within 28 days of the dose interruption period or if the patient has already undergone dose reduction to 100 mg once daily.a
Hematologic adverse reaction requiring transfusion | - For patients with platelet count ≤10,000/mcL, platelet transfusion should be considered. If there are other risk factors such as coadministration of anticoagulation or antiplatelet drugs, consider interrupting these drugs and/or transfusion at a higher platelet count. - Resume ZEJULA at a reduced dose per Table 1.
a If myelodysplastic syndrome or acute myeloid leukemia (MDS/AML) is confirmed, discontinue ZEJULA [see Warnings and Precautions (5.1, 5.2)].

2.4 Dosage Modifications for Hepatic Impairment

For patients with moderate hepatic impairment (total bilirubin ≥1.5 to 3 x ULN and any AST level), the recommended dosage of ZEJULA is 200 mg once daily, regardless of body weight or platelet count [see Use in Specific Populations (8.6), Clinical Pharmacology (12.3)]. Monitor patients for hematologic toxicity and reduce the dose, if needed [see Dosage and Administration (2.3)].

3 DOSAGE FORMS AND STRENGTHS

- Tablets: 100-mg gray, oval-shaped, film-coated tablet debossed with “100” on one side and “Zejula” on the other side.
- Tablets: 200-mg blue, oval-shaped, film-coated tablet debossed with “200” on one side and “Zejula” on the other side.
- Tablets: 300-mg green, oval-shaped, film-coated tablet debossed with “300” on one side and “Zejula” on the other side.

4 CONTRAINDICATIONS

None.

5 WARNINGS AND PRECAUTIONS

5.1 Myelodysplastic Syndrome/Acute Myeloid Leukemia

Myelodysplastic syndrome/acute myeloid leukemia (MDS/AML), including cases with a fatal outcome, have been reported in patients who received ZEJULA.

In PRIMA, of patients within the HRD-positive population, MDS/AML occurred in 8 out of 245 (3.3%) patients treated with ZEJULA and in 3 out of 125 (2.4%) patients treated with placebo with a follow-up of 6.1 years [see Adverse Reactions (6.1)]. The duration of therapy with ZEJULA in patients who developed secondary MDS/cancer-therapy–related AML varied from 5.5 months to 5 years.

In NOVA, of patients within the gBRCAmut cohort, MDS/AML occurred in 10 out of 136 (7%) patients treated with ZEJULA and in 2 out of 65 (3%) patients treated with placebo [see Adverse Reactions (6.1)]. The duration of therapy with ZEJULA in patients who developed secondary MDS/cancer-therapy–related AML varied from 3.6 months to 5.9 years.

All patients who developed secondary MDS/cancer-therapy–related AML had received previous chemotherapy with platinum agents and/or other DNA-damaging agents, including radiotherapy.

For suspected MDS/AML or prolonged hematological toxicities, refer the patient to a hematologist for further evaluation. Discontinue ZEJULA if MDS/AML is confirmed.

5.2 Bone Marrow Suppression

Hematologic adverse reactions, including thrombocytopenia, anemia, neutropenia, and/or pancytopenia have been reported in patients treated with ZEJULA [see Adverse Reactions (6)].

In PRIMA, the overall incidences of ≥Grade 3 thrombocytopenia, anemia, and neutropenia were reported in 39%, 31%, and 21%, respectively, of patients receiving ZEJULA. Discontinuation due to thrombocytopenia, anemia, and neutropenia occurred in 4%, 2%, and 2%, respectively, of patients. In patients who were administered a starting dose of ZEJULA based on baseline weight or platelet count, ≥Grade 3 thrombocytopenia, anemia, and neutropenia were reported in 22%, 23%, and 15%, respectively, of patients receiving ZEJULA. Discontinuation due to thrombocytopenia, anemia, and neutropenia occurred in 3%, 3%, and 2%, respectively, of patients.

In NOVA, ≥Grade 3 thrombocytopenia, anemia, and neutropenia were reported in 29%, 25%, and 20%, respectively, of patients receiving ZEJULA. Discontinuation due to thrombocytopenia, anemia, and neutropenia occurred in 3%, 1%, and 2%, respectively, of patients.

Do not start ZEJULA until patients have recovered from hematological toxicity caused by previous chemotherapy (≤Grade 1). Monitor complete blood counts weekly for the first month, monthly for the next 11 months of treatment, and periodically after this time. If hematological toxicities do not resolve within 28 days following interruption, discontinue ZEJULA and refer the patient to a hematologist for further investigations, including bone marrow analysis and blood sample for cytogenetics [see Dosage and Administration (2.3)].

5.3 Hypertension and Cardiovascular Effects

Hypertension and hypertensive crisis have been reported in patients treated with ZEJULA [see Adverse Reactions (6)].

In PRIMA, Grade 3 to 4 hypertension occurred in 6% of patients treated with ZEJULA compared with 1% of placebo-treated patients with a median time from first dose to first onset of 43 days (range: 1 to 531 days) and with a median duration of 12 days (range: 1 to 61 days). There were no discontinuations due to hypertension.

In NOVA, Grade 3 to 4 hypertension occurred in 9% of patients treated with ZEJULA compared with 2% of placebo-treated patients with a median time from first dose to first onset of 77 days (range: 4 to 504 days) and with a median duration of 15 days (range: 1 to 86 days). Discontinuation due to hypertension occurred in <1% of patients.

Monitor blood pressure and heart rate at least weekly for the first 2 months, then monthly for the first year and periodically thereafter during treatment with ZEJULA. Closely monitor patients with cardiovascular disorders, especially coronary insufficiency, cardiac arrhythmias, and hypertension. Medically manage hypertension with antihypertensive medications and adjustment of the dose of ZEJULA, if necessary [see Dosage and Administration (2.3), Nonclinical Toxicology (13.2)].

5.4 Posterior Reversible Encephalopathy Syndrome

Posterior reversible encephalopathy syndrome (PRES) occurred in 0.1% of 2,165 patients treated with ZEJULA in clinical trials and has also been described in postmarketing reports [see Adverse Reactions (6.2)]. Signs and symptoms of PRES include seizure, headache, altered mental status, visual disturbance, or cortical blindness, with or without associated hypertension. A diagnosis of PRES requires confirmation by brain imaging, preferably magnetic resonance imaging.

Monitor all patients treated with ZEJULA for signs and symptoms of PRES. If PRES is suspected, promptly discontinue ZEJULA and administer appropriate treatment. The safety of reinitiating ZEJULA in patients previously experiencing PRES is not known.

5.5 Embryo-Fetal Toxicity

Based on its mechanism of action, ZEJULA can cause fetal harm when administered to a pregnant woman [see Clinical Pharmacology (12.1)]. ZEJULA has the potential to cause teratogenicity and/or embryo-fetal death since niraparib is genotoxic and targets actively dividing cells in animals and patients (e.g., bone marrow) [see Warnings and Precautions (5.2), Nonclinical Toxicology (13.1)]. Due to the potential risk to a fetus based on its mechanism of action, animal developmental and reproductive toxicology studies were not conducted with niraparib.

Apprise pregnant women of the potential risk to a fetus. Advise females of reproductive potential to use effective contraception during treatment and for 6 months after the last dose of ZEJULA [see Use in Specific Populations (8.1, 8.3)].

6 ADVERSE REACTIONS

The following clinically significant adverse reactions are described elsewhere in the labeling:

- MDS/AML [see Warnings and Precautions (5.1)]
- Bone marrow suppression [see Warnings and Precautions (5.2)]
- Hypertension and cardiovascular effects [see Warnings and Precautions (5.3)]
- Posterior reversible encephalopathy syndrome [see Warnings and Precautions (5.4)]

6.1 Clinical Trials Experience

Because clinical trials are conducted under widely varying conditions, adverse reaction rates observed in the clinical trials of a drug cannot be directly compared with rates in the clinical trials of another drug and may not reflect the rates observed in practice.

In a pooled safety population of patients (n = 1,314) with advanced ovarian, fallopian tube, or primary peritoneal cancer treated with ZEJULA monotherapy including PRIMA (n = 484), NOVA (n = 367), and another clinical trial (n = 463), the most common adverse reactions >10% were nausea (65%), thrombocytopenia (60%), anemia (56%), fatigue (55%), constipation (39%), musculoskeletal pain (36%), abdominal pain (35%), vomiting (33%), neutropenia (31%), decreased appetite (24%), leukopenia (24%), insomnia (23%), headache (23%), dyspnea (22%), rash (21%), diarrhea (18%), hypertension (17%), cough (16%), dizziness (14%), acute kidney injury (13%), urinary tract infection (12%), and hypomagnesemia (11%).

First-Line Maintenance Treatment of HRD-Positive Advanced Ovarian Cancer

The safety of ZEJULA for the treatment of patients with advanced ovarian cancer following first-line treatment with platinum-based chemotherapy was studied in the PRIMA trial, a placebo-controlled, double-blind study in which 484 patients received ZEJULA. Among this population, 245 patients were HRD-positive and their median duration of treatment was 13 months (range: 3 days to 29 months).

HRD-Positive Patients Receiving ZEJULA in PRIMA: Serious adverse reactions occurred in 30% of patients receiving ZEJULA. Serious adverse reactions in >2% of patients were thrombocytopenia (11%) and anemia (5%). Fatal adverse reactions occurred in 1.6% of patients, including AML (0.4%), cardiac arrest (0.4%), intestinal perforation (0.4%), and sudden death (0.4%).

Permanent discontinuation due to adverse reactions occurred in 11% of patients who received ZEJULA. Adverse reactions resulting in permanent discontinuation in >1% of patients who received ZEJULA included thrombocytopenia (3.7%), nausea (1.6%), and anemia (1.2%).

Adverse reactions led to dose reduction or interruption in 79% of patients, most frequently (>10%) from thrombocytopenia (53%), anemia (32%), and neutropenia (19%).

Tables 4 and 5 summarize the common adverse reactions and abnormal laboratory findings observed in the PRIMA trial.

Table 4. Adverse Reactions Reported in ≥10% of HRD-Positive Patients Receiving ZEJULA in PRIMAa
Adverse Reaction | Grades 1-4b |  | Grades 3-4b
Adverse Reaction | ZEJULA; (n = 245); % | Placebo; (n = 125); % | ZEJULA; (n = 245); % | Placebo; (n = 125); %
Blood and lymphatic system disorders
Thrombocytopenia | 66 | 4 | 38 | 0
Anemia | 65 | 16 | 31 | 2
Neutropeniac | 43 | 9 | 17 | 2
Leukopeniad | 29 | 10 | 6 | 0.8
Gastrointestinal disorders
Nausea | 62 | 34 | 1 | 0
Constipation | 40 | 26 | 1 | 0.8
Vomiting | 23 | 14 | 2 | 0.8
General disorders and administration site conditions
Fatigue | 52 | 44 | 2 | 2
Musculoskeletal and connective tissue disorders
Musculoskeletal pain | 46 | 38 | 0.8 | 0
Nervous system disorders
Headache | 27 | 15 | 0.8 | 0
Dizziness | 20 | 11 | 0 | 0
Psychiatric disorders
Insomnia | 25 | 16 | 0.4 | 0.8
Anxiety | 12 | 6 | 0 | 0
Respiratory, thoracic, and mediastinal disorders
Dyspnea | 21 | 15 | 0 | 0.8
Cough | 20 | 14 | 0 | 0.8
Metabolism and nutrition disorders
Decreased appetite | 20 | 6 | 0.4 | 0
Vascular disorders
Hypertension | 20 | 8 | 7 | 2
Investigations
AST/ALT elevation | 14 | 8 | 3 | 0
Renal and urinary disorders
Acute kidney injurye | 13 | 3 | 0 | 0
AST/ALT = Aspartate aminotransferase/alanine aminotransferase.
a All adverse reactions in the table consist of grouped preferred terms except for nausea, vomiting, decreased appetite, headache, and insomnia, which are single preferred terms.
b Common Terminology Criteria for Adverse Events version 4.02.
c Includes neutropenia, neutropenic infection, neutropenic sepsis, and febrile neutropenia.
d Includes leukopenia, lymphocyte count decreased, lymphopenia, and white blood cell count decreased.
e Includes blood creatinine increased, blood urea increased, acute kidney injury, and renal failure.

Table 5. Abnormal Laboratory Findings in ≥25% of HRD-Positive Patients Receiving ZEJULA in PRIMA
Abnormal Laboratory Finding | Grades 1-4 |  | Grades 3-4
Abnormal Laboratory Finding | ZEJULA; (n = 245); % | Placebo; (n = 125); % | ZEJULA; (n = 245); % | Placebo; (n = 125); %
Decreased hemoglobin | 85 | 65 | 28 | 2
Decreased leukocytes | 72 | 37 | 9 | 0
Decreased platelets | 71 | 11 | 36 | 0
Decreased neutrophils | 64 | 28 | 21 | 2
Increased glucose | 62 | 57 | 3 | 4
Decreased lymphocytes | 55 | 26 | 9 | 5
Increased alkaline phosphatase | 48 | 19 | 2 | 0.8
Increased creatinine | 40 | 24 | 0 | 0
Decreased magnesium | 39 | 35 | 0.4 | 0
Increased aspartate aminotransferase | 35 | 18 | 2 | 0.8
Increased alanine aminotransferase | 32 | 19 | 2 | 2
Increased calcium | 31 | 23 | 1 | 0

HRD-Positive Patients Receiving ZEJULA with Dose Based on Baseline Weight or Platelet Count in PRIMA: Among patients who received ZEJULA with the dose based on weight and platelet count (n = 86), the median duration of treatment was 12 months (range: 4 days to 16 months).

Serious adverse reactions occurred in 24% of patients receiving ZEJULA. Serious adverse reactions in >2% of patients were anemia (9%) and thrombocytopenia (2%).

Permanent discontinuation due to adverse reactions occurred in 11% of patients who received ZEJULA. Adverse reactions resulting in permanent discontinuation in >2% of patients who received ZEJULA included nausea (3.5%).

Adverse reactions led to dose reduction or interruption in 72% of patients, most frequently (>10%) from thrombocytopenia (35%), anemia (22%), and neutropenia (17%).

Tables 6 and 7 summarize adverse reactions and abnormal laboratory findings observed in this group.

Table 6. Adverse Reactions Reported in ≥10% of HRD-Positive Patients Receiving ZEJULA Based on Baseline Weight or Platelet Count in PRIMAa
Adverse Reaction | Grades 1-4b |  | Grades 3-4b
Adverse Reaction | ZEJULA; (n = 86); % | Placebo; (n = 42); % | ZEJULA; (n = 86); % | Placebo; (n = 42); %
Blood and lymphatic system disorders
Thrombocytopenia | 51 | 2 | 16 | 0
Anemia | 49 | 21 | 22 | 0
Neutropeniac | 35 | 7 | 13 | 0
Leukopeniad | 26 | 7 | 6 | 0
Gastrointestinal disorders
Nausea | 55 | 21 | 0 | 0
Constipation | 26 | 29 | 1 | 2
Vomiting | 16 | 17 | 0 | 2.4
General disorders and administration site conditions
Fatigue | 47 | 41 | 0 | 0
Nervous system disorders
Headache | 24 | 19 | 1 | 0
Dizziness | 15 | 7 | 0 | 0
Psychiatric disorders
Insomnia | 21 | 19 | 0 | 0
Metabolism and nutrition disorders
Decreased appetite | 19 | 7 | 1 | 0
Respiratory, thoracic, and mediastinal disorders
Dyspnea | 20 | 12 | 0 | 2
Vascular disorders
Hypertension | 16 | 12 | 4 | 5
Renal and urinary disorders
Acute kidney injurye | 14 | 2 | 0 | 0
a All adverse reactions in the table consist of grouped preferred terms except for nausea, vomiting, decreased appetite, headache, and insomnia, which are single preferred terms.
b Common Terminology Criteria for Adverse Events version 4.02.
c Includes neutropenia, neutropenic infection, neutropenic sepsis, and febrile neutropenia.
d Includes leukopenia, lymphocyte count decreased, lymphopenia, and white blood cell count decreased.
e Includes blood creatinine increased, blood urea increased, acute kidney injury, and renal failure.

Table 7. Abnormal Laboratory Findings in ≥25% of HRD-Positive Patients Receiving ZEJULA Based on Baseline Weight or Platelet Count in PRIMA
Abnormal Laboratory Finding | Grades 1-4 |  | Grades 3-4
Abnormal Laboratory Finding | ZEJULA; (n = 86); % | Placebo; (n = 42); % | ZEJULA; (n = 86); % | Placebo; (n = 42); %
Decreased hemoglobin | 74 | 67 | 21 | 0
Decreased leukocytes | 70 | 36 | 6 | 0
Decreased platelets | 58 | 17 | 14 | 0
Increased glucose | 57 | 62 | 4 | 2
Decreased neutrophils | 57 | 31 | 13 | 0
Decreased lymphocytes | 55 | 24 | 6 | 5
Decreased magnesium | 51 | 41 | 0 | 0
Increased alkaline phosphatase | 42 | 12 | 2 | 0
Increased creatinine | 42 | 24 | 0 | 0
Increased aspartate aminotransferase | 31 | 21 | 2 | 0
Increased alanine aminotransferase | 30 | 17 | 2 | 2
Increased calcium | 29 | 36 | 0 | 0

Maintenance Treatment of Recurrent Germline BRCA-mutated Ovarian Cancer

The safety of monotherapy with ZEJULA 300 mg once daily has been studied in 136 patients with platinum-sensitive recurrent gBRCAmut ovarian, fallopian tube, and primary peritoneal cancer in the NOVA trial. The percentages of patients who experienced adverse reactions in NOVA that led to dose reduction and dose interruption were 79% and 68%, respectively, most frequently from thrombocytopenia (41% and 35%, respectively) and anemia (23% and 20%, respectively). The permanent discontinuation rate due to adverse reactions in NOVA was 13%. The median exposure to ZEJULA in these patients was 367 days.

Table 8 and Table 9 summarize the common adverse reactions and abnormal laboratory findings, respectively, observed in patients treated with ZEJULA in the gBRCAmut cohort in NOVA.

Table 8. Adverse Reactions Reported in ≥10% of Patients Receiving ZEJULA in NOVA gBRCAmut Cohort
Adverse Reaction | Grades 1-4a |  | Grades 3-4a
Adverse Reaction | ZEJULA; (n = 136); % | Placebo; (n = 65); % | ZEJULA; (n = 136); % | Placebo; (n = 65); %
Gastrointestinal disorders
Nausea | 77 | 34 | 5 | 3
Vomiting | 40 | 15 | 4 | 0
Constipation | 38 | 18 | 0.7 | 2
Dyspepsia | 17 | 12 | 0 | 0
Dry mouth | 13 | 3 | 0.7 | 0
Blood and lymphatic system disorders
Thrombocytopeniab | 71 | 5 | 38 | 2
Anemiac | 52 | 8 | 33 | 0
Neutropeniad | 31 | 9 | 21 | 3
General disorders and administration site conditions
Fatiguee | 61 | 35 | 8 | 2
Nervous system disorders
Headache | 35 | 8 | 0.7 | 0
Dizziness | 18 | 9 | 0 | 0
Dysgeusia | 13 | 2 | 0 | 0
Metabolism and nutrition disorders
Decreased appetite | 22 | 14 | 0 | 0
Vascular disorders
Hypertension | 21 | 8 | 8 | 5
Psychiatric disorders
Insomnia | 18 | 6 | 0.7 | 0
Anxiety | 10 | 11 | 0.7 | 0
Respiratory, thoracic, and mediastinal disorders
Dyspnea | 17 | 5 | 2 | 0
Cough | 16 | 2 | 0 | 0
Nasopharyngitis | 13 | 5 | 0 | 0
Musculoskeletal and connective tissue disorders
Back pain | 16 | 11 | 0.7 | 0
Infections and infestations
Urinary tract infection | 11 | 9 | 0 | 2
Skin and subcutaneous tissue disorders
Rash | 10 | 2 | 0 | 0
gBRCAmut = Germline BRCA-mutated.
a Common Terminology Criteria for Adverse Events version 4.02.
b Includes platelet count decreased.
c Includes hemoglobin decreased.
d Includes neutrophil count decreased.
e Includes asthenia, malaise, and lethargy.

The following adverse reactions have been identified in ≥1 to <10% of the 136 patients receiving ZEJULA in the gBRCAmut cohort of the NOVA trial and not included in the table: palpitations (9%), mucositis/stomatitis (9%), MDS/AML (7%), tachycardia (7%), and bronchitis (4%).

Table 9. Abnormal Laboratory Findings in ≥25% of Patients Receiving ZEJULA in NOVA gBRCAmut Cohort
Abnormal Laboratory Finding | Grades 1-4 |  | Grades 3-4
Abnormal Laboratory Finding | ZEJULA; (n = 136); % | Placebo; (n = 65); % | ZEJULA; (n = 136); % | Placebo; (n = 65); %
Decrease in hemoglobin | 85 | 62 | 32 | 0
Decrease in platelet count | 81 | 25 | 38 | 2
Decrease in white blood cell count | 71 | 37 | 9 | 2
Decrease in absolute neutrophil count | 56 | 34 | 23 | 3
Increase in aspartate aminotransferase | 35 | 25 | 0.7 | 0
Increase in alanine aminotransferase | 25 | 15 | 0.7 | 2
gBRCAmut = Germline BRCA-mutated.

6.2 Postmarketing Experience

The following adverse reactions have been identified during postapproval use of ZEJULA. Because these reactions are reported voluntarily from a population of uncertain size, it is not always possible to reliably estimate their frequency or establish a causal relationship to drug exposure.

Blood and Lymphatic System Disorders

Pancytopenia.

Immune System Disorders

Hypersensitivity (including anaphylaxis).

Nervous System Disorders

Posterior reversible encephalopathy syndrome (PRES).

Psychiatric Disorders

Confusional state/disorientation, hallucination, cognitive impairment (e.g., memory impairment, concentration impairment).

Respiratory, Thoracic, and Mediastinal Disorders

Non-infectious pneumonitis.

Skin and Subcutaneous Tissue Disorders

Photosensitivity.

Vascular Disorders

Hypertensive crisis.

8 USE IN SPECIFIC POPULATIONS

8.1 Pregnancy

Risk Summary

Based on its mechanism of action, ZEJULA can cause fetal harm when administered to pregnant women [see Clinical Pharmacology (12.1)]. There are no data regarding the use of ZEJULA in pregnant women to inform the drug-associated risk. ZEJULA has the potential to cause teratogenicity and/or embryo-fetal death since niraparib is genotoxic and targets actively dividing cells in animals and patients (e.g., bone marrow) [see Warnings and Precautions (5.2), Nonclinical Toxicology (13.1)]. Due to the potential risk to a fetus based on its mechanism of action, animal developmental and reproductive toxicology studies were not conducted with niraparib. Apprise pregnant women of the potential risk to a fetus.

The background risk of major birth defects and miscarriage for the indicated population is unknown. In the U.S. general population, the estimated background risk of major birth defects and miscarriage in clinically recognized pregnancies is 2% to 4% and 15% to 20%, respectively.

8.2 Lactation

Risk Summary

No data are available regarding the presence of niraparib or its metabolites in human milk, or on its effects on the breastfed child or milk production. Because of the potential for serious adverse reactions in a breastfed child, advise a lactating woman not to breastfeed during treatment with ZEJULA and for 1 month after receiving the last dose.

8.3 Females and Males of Reproductive Potential

ZEJULA can cause fetal harm when administered to a pregnant woman [see Use in Specific Populations (8.1)].

Pregnancy Testing

Verify the pregnancy status of females of reproductive potential prior to initiating treatment with ZEJULA.

Contraception

Females: Advise females of reproductive potential to use effective contraception during treatment with ZEJULA and for 6 months following the last dose.

Infertility

Males: Based on animal studies, ZEJULA may impair fertility in males of reproductive potential [see Nonclinical Toxicology (13.1)].

8.4 Pediatric Use

The safety and effectiveness of ZEJULA have not been established in pediatric patients.

8.5 Geriatric Use

In PRIMA, 39% of patients were aged 65 years or older and 10% were aged 75 years or older. In NOVA, 35% of patients were aged 65 years or older and 8% were aged 75 years or older. No overall differences in safety and effectiveness of ZEJULA were observed between these patients and younger patients but greater sensitivity of some older individuals cannot be ruled out.

8.6 Hepatic Impairment

For patients with moderate hepatic impairment, the recommended dosage of ZEJULA is 200 mg once daily, regardless of body weight or platelet count. Monitor patients for hematologic toxicity and reduce the dose, if needed [see Dosage and Administration (2.3, 2.4)]. Niraparib exposure increased in patients with moderate hepatic impairment (total bilirubin ≥1.5 to 3 x ULN and any AST level).

For patients with mild hepatic impairment (total bilirubin <1.5 x ULN and any AST level or bilirubin ≤ULN and AST >ULN), no dosage modification is recommended.

The effect of severe hepatic impairment (total bilirubin >3 x ULN and any AST level) on niraparib pharmacokinetics is unknown.

11 DESCRIPTION

Niraparib is an orally available poly (ADP-ribose) polymerase (PARP) inhibitor.

The chemical name for niraparib tosylate monohydrate is 2-{4-[(3S)-piperidin-3-yl]phenyl}-2H-indazole 7-carboxamide 4-methylbenzenesulfonate hydrate (1:1:1). The molecular formula is C26H30N4O5S and it has a molecular weight of 510.61 amu. The molecular structure is shown below:

Niraparib tosylate monohydrate is a white to off-white, non-hygroscopic crystalline solid. Niraparib solubility is pH independent below the pKa of 9.95, with an aqueous free base solubility of 0.7 mg/mL to 1.1 mg/mL across the physiological pH range.

Each ZEJULA tablet contains 159.3 mg, 318.7 mg, or 478.0 mg of niraparib tosylate monohydrate equivalent to 100 mg, 200 mg, or 300 mg, respectively, of niraparib free base as the active ingredient. The inactive ingredients in the core tablet are crospovidone, lactose monohydrate, magnesium stearate, microcrystalline cellulose, povidone, and silicon dioxide. The film-coating consists of Opadry II Gray (100 mg), Opadry II Blue (200 mg), or Opadry II Green (300 mg).

12 CLINICAL PHARMACOLOGY

12.1 Mechanism of Action

Niraparib is an inhibitor of PARP enzymes, including PARP-1 and PARP-2, that play a role in DNA repair. In vitro studies have shown that niraparib-induced cytotoxicity may involve inhibition of PARP enzymatic activity and increased formation of PARP-DNA complexes resulting in DNA damage, apoptosis, and cell death. Increased niraparib‑induced cytotoxicity was observed in tumor cell lines with or without deficiencies in BRCA1/2. Niraparib decreased tumor growth in mouse xenograft models of human cancer cell lines with deficiencies in BRCA1/2 and in human patient-derived xenograft tumor models with homologous recombination deficiency (HRD) that had either mutated or wild-type BRCA1/2.

12.2 Pharmacodynamics

The pharmacodynamic response of niraparib has not been characterized.

Hypertension and Cardiovascular Effects

Niraparib has the potential to cause effects on pulse rate and blood pressure in patients receiving the recommended dose, which may be related to pharmacological inhibition of the dopamine transporter, norepinephrine transporter, and serotonin transporter [see Nonclinical Toxicology (13.2)].

In PRIMA, mean pulse rate and blood pressure increased over baseline in the niraparib arm relative to the placebo arm at most on-study assessments. Mean greatest increases from baseline in pulse rate on treatment were 22.4 and 14.0 beats/min in the niraparib and placebo arms, respectively. Mean greatest increases from baseline in systolic blood pressure on treatment were 24.4 and 19.6 mmHg in the niraparib and placebo arms, respectively. Mean greatest increases from baseline in diastolic blood pressure on treatment were 15.9 and 13.9 mmHg in the niraparib and placebo arms, respectively.

In NOVA, mean pulse rate and blood pressure increased over baseline in the niraparib arm relative to the placebo arm at all on-study assessments. Mean greatest increases from baseline in pulse rate on treatment were 24.1 and 15.8 beats/min in the niraparib and placebo arms, respectively. Mean greatest increases from baseline in systolic blood pressure on treatment were 24.5 and 18.3 mmHg in the niraparib and placebo arms, respectively. Mean greatest increases from baseline in diastolic blood pressure on treatment were 16.5 and 11.6 mmHg in the niraparib and placebo arms, respectively.

Cardiac Electrophysiology

At the approved maximum recommended dose, a mean increase in the QTc interval >20 ms was not observed.

12.3 Pharmacokinetics

Niraparib mean (±SD) maximum plasma concentration (Cmax) is 603 (±343) ng/mL at the approved maximum recommended dose of 300 mg. Niraparib steady-state Cmax and AUC increased in a dose-proportional manner with daily doses ranging from 30 mg (0.15 times the approved minimum recommended dose) to 400 mg (1.3 times the approved maximum recommended dose). The accumulation of niraparib exposure is approximately 2-fold at the approved recommended doses.

Absorption

The absolute bioavailability of niraparib is approximately 73%. Time to maximum plasma concentration (Tmax) is reached within 5 hours.

Food Effect: Niraparib Cmax increased by 11% and AUC by 28%, following administration with a high-fat meal (800 to 1,000 calories, 50% fat).

Distribution

Niraparib is 83% bound to human plasma proteins. Niraparib mean (±SD) apparent (oral) volume of distribution (Vd/F) is 1,220 (±1,114) L.

Elimination

Niraparib apparent (oral) total clearance (CL/F) is 15.9 (±3.8) L/h and mean half-life (t1/2) is 50 (±15) hours.

Metabolism: Niraparib is metabolized by carboxylesterases to form a major inactive metabolite M1, which subsequently undergoes glucuronidation.

Excretion: Following administration of a single oral dose of radio-labeled niraparib 300 mg, 48% of the dose was recovered in urine (11% unchanged) and 39% in feces (19% unchanged).

Specific Populations

No clinically significant differences in the pharmacokinetics of niraparib were observed based on age (18 to 65 years), race/ethnicity, and mild to moderate renal impairment (CLcr 30 to 90 mL/min).

The effect of severe renal impairment (CLcr <30 mL/min) or end-stage renal disease undergoing hemodialysis on the pharmacokinetics of niraparib is unknown.

Hepatic Impairment: Mild hepatic impairment (total bilirubin <1.5 x ULN and any AST level or bilirubin ≤ULN and AST >ULN) had no clinically significant effect on the pharmacokinetics of niraparib.

Niraparib AUC increased 1.6-fold in patients with moderate hepatic impairment (total bilirubin ≥1.5 to 3 x ULN and any AST level) with no effect on niraparib Cmax or protein binding.

The effect of severe hepatic impairment (total bilirubin >3 x ULN and any AST level) on the pharmacokinetics of niraparib is unknown.

Drug Interaction Studies

In Vitro Studies:

Cytochrome P450 (CYP) Enzymes: Niraparib and M1 did not inhibit CYP1A, CYP2B6, CYP2C8, CYP2C9, CYP2C19, CYP2D6, and CYP3A.

Niraparib and M1 do not induce CYP3A.

Uridine 5'-Diphospho-Glucuronosyltransferases (UGTs): Niraparib did not inhibit UGT1A1, UGT1A4, UGT1A9, and UGT2B7.

Transporters: Niraparib inhibits BCRP, MATE1, and MATE2K, but does not inhibit P-glycoprotein (P-gp), BSEP, or MRP2.

M1 did not inhibit P-gp, BCRP, BSEP, MRP2, MATE1 or MATE2K. Niraparib and M1 did not inhibit OATP1B1, OATP1B3, OCT1, OAT1, OAT3, or OCT2.

Niraparib is a substrate of P-gp and BCRP, but not of BSEP, MRP2, MATE1, MATE2K, OATP1B1, OATP1B3, OCT1, OAT1, OAT3, or OCT2.

M1 is a substrate of MATE1 and MATE2K, but not of P-gp, BCRP, BSEP, MRP2, OATP1B1, OATP1B3, OCT1, OAT1, OAT3, or OCT2.

13 NONCLINICAL TOXICOLOGY

13.1 Carcinogenesis, Mutagenesis, Impairment of Fertility

Carcinogenicity studies have not been conducted with niraparib.

Niraparib was clastogenic in an in vitro mammalian chromosomal aberration assay and in an in vivo rat bone marrow micronucleus assay. This clastogenicity is consistent with genomic instability resulting from the primary pharmacology of niraparib and indicates potential for genotoxicity in humans. Niraparib was not mutagenic in a bacterial reverse mutation assay (Ames) test.

Fertility studies in animals have not been conducted with niraparib. In repeat-dose oral toxicity studies, niraparib was administered daily for up to 3 months’ duration in rats and dogs. Reduced sperm, spermatids, and germ cells in epididymides and testes were observed at doses ≥10 mg/kg and ≥1.5 mg/kg in rats and dogs, respectively. These dose levels resulted in systemic exposures approximately 0.3 and 0.012 times, respectively, the human exposure (AUC0-24h) at the recommended dose of 300 mg daily. There was a trend toward reversibility of these findings 4 weeks after dosing was stopped.

13.2 Animal Toxicology and/or Pharmacology

In vitro, niraparib bound to DAT, NET, and SERT and inhibited uptake of norepinephrine and dopamine in cells with IC50 values that were lower than the Cmin at steady-state in patients receiving the recommended dose. Niraparib has the potential to cause effects in patients related to inhibition of these transporters (e.g., cardiovascular, central nervous system).

Intravenous administration of niraparib to vagotomized dogs over 30 minutes at 1, 3, and 10 mg/kg resulted in an increased range of arterial pressures of 13% to 20%, 18% to 27%, and 19% to 25%, respectively, and increased range of heart rates of 2% to 11%, 4% to 17%, and 12% to 21%, respectively, above pre-dose levels. The unbound plasma concentrations of niraparib in dogs at these dose levels were approximately 0.5, 1.5, and 5.8 times the unbound Cmax at steady‑state in patients receiving the recommended dose.

In addition, niraparib crossed the blood-brain barrier in rats and monkeys following oral administration. The cerebrospinal fluid:plasma Cmax ratios of niraparib administered at 10 mg/kg orally to 2 rhesus monkeys were 0.10 and 0.52.

14 CLINICAL STUDIES

14.1 First-Line Maintenance Treatment of HRD-Positive Advanced Ovarian Cancer

PRIMA (NCT02655016) was a double-blind, placebo-controlled trial in which patients (N = 733) in complete or partial response to first-line platinum-based chemotherapy were randomized 2:1 to ZEJULA or matched placebo. Initially, the patients received a starting dosage of 300 mg once daily regardless of body weight or platelet count. The study was amended to include a starting dose of 200 mg for patients weighing <77 kg (<170 lbs) OR with a platelet count of <150,000/mcL or 300 mg for patients weighing ≥77 kg (≥170 lbs) AND who had a platelet count ≥150,000/mcL.

Patients were randomized post-completion of first-line platinum-based chemotherapy plus surgery. Randomization was stratified by best response during the front-line platinum regimen (complete response vs. partial response), neoadjuvant chemotherapy (NACT) (yes vs. no), and HRD status (positive vs. negative or not determined). HRD status was determined using an investigational HRD assay. HRD-positive status included either tumor BRCA mutant (tBRCAm) or a genomic instability score (GIS) ≥42.

The major efficacy outcome measure, progression-free survival (PFS), was determined by blinded independent central review (BICR) per Response Evaluation Criteria in Solid Tumors (RECIST) version 1.1. In some cases, criteria other than RECIST, such as clinical signs and symptoms and increasing CA-125, were also applied. Overall survival (OS) was an additional efficacy outcome measure.

Efficacy was evaluated in 373 patients in the HRD-positive population. The median age was 58 years (range 32 to 83 years). Eighty-seven percent of patients were White, 4.8% were Asian, 1.6% were Black or African American, 0.3% were Native Hawaiian or Other Pacific Islander, and 0.3% were American Indian or Alaska Native. Six percent of patients were Hispanic or Latino. Seventy-five percent of patients had an Eastern Cooperative Oncology Group Performance Status (ECOG PS) of 0 at trial baseline. Approximately 47% of patients were enrolled in the U.S. or Canada. Sixty-four percent of patients had Stage III disease and 36% had Stage IV disease. Sixty-three percent of the patients received NACT. Seventy-five percent of the patients had a complete response to the first-line platinum-based chemotherapy. Approximately 35% (n = 130) of patients received a starting dose of 200 or 300 mg depending on baseline body weight and platelet count.

PRIMA demonstrated a statistically significant improvement in PFS for patients randomized to ZEJULA as compared with placebo in the HRD-positive population (Table 10 and Figure 1).

Table 10. Efficacy Results – PRIMA HRD-Positive Population Progression-Free Survival (PFS)a
 | ZEJULA; (n = 247) | Placebo; (n = 126)
PFS events, n (%) | 81 (33) | 73 (58)
PFS median in months (95% CI) | 21.9; (19.3, NE) | 10.4; (8.1, 12.1)
Hazard ratiob (95% CI) | 0.43; (0.31, 0.59)
P valuec | <0.0001
HRD = Homologous Recombination Deficient; NE = Not Estimable.
a Efficacy analysis was based on blinded independent central review.
b Based on a stratified Cox proportional hazards model.
c Based on a stratified log-rank test.

In an exploratory subgroup analysis of patients in the HRD-positive population who were administered a starting dose of ZEJULA or matched placebo based on baseline weight or platelet count (n = 130), the hazard ratio (HR) for PFS was 0.39 (95% CI: 0.22, 0.72).

Figure 1. PRIMA Progression-Free Survival – HRD-Positive Population

HRD = Homologous Recombination Deficient.

A final OS analysis was conducted in the HRD-positive population after 185 events were observed; the HR was 0.95 (95% CI: 0.71, 1.29) with a median OS of 71.9 months (95% CI: 55.5, NE) for patients treated with ZEJULA and 69.8 months (95% CI: 51.6, NE) for patients on placebo.

14.2 Maintenance Treatment of Recurrent Germline BRCA-Mutated Ovarian Cancer

NOVA (NCT01847274) was a double-blind, placebo-controlled trial in which patients (N = 553) with platinum-sensitive recurrent epithelial ovarian, fallopian tube, or primary peritoneal cancer were randomized 2:1 to ZEJULA 300 mg orally daily or matched placebo within 8 weeks of the last therapy. Treatment was continued until disease progression or unacceptable toxicity. All patients had received at least 2 prior platinum-containing regimens and were in response (complete or partial) to their most recent platinum-based regimen.

Randomization was stratified by time to progression after the penultimate platinum therapy (6 to <12 months and ≥12 months), use of bevacizumab in conjunction with the penultimate or last platinum regimen (yes/no), and best response during the most recent platinum regimen (complete response and partial response). Eligible patients were assigned to 1 of 2 cohorts based on the results of germline BRCA testing with Myriad BRACAnalysis CDx. Patients with deleterious or suspected deleterious germline BRCA mutations (gBRCAmut) were assigned to the germline BRCA-mutated (gBRCAmut) cohort (n = 203), and those without germline BRCA mutations were assigned to the non-gBRCAmut cohort (n = 350). The efficacy results are based on the gBRCAmut cohort only.

The major efficacy outcome measure, PFS, was determined primarily by central independent assessment per RECIST version 1.1. In some cases, criteria other than RECIST, such as clinical signs and symptoms and increasing CA-125, were also applied. Overall survival (OS) was an additional outcome measure.

For the gBRCAmut cohort, the median age of patients was 57 years among patients treated with ZEJULA and 58 years among patients treated with placebo. Eighty-eight percent of all patients were White. Sixty-six percent of patients receiving ZEJULA and 74% of patients receiving placebo had an ECOG PS of 0 at study baseline. Approximately 40% of patients were enrolled in the U.S. or Canada, and 51% of all patients were in complete response to most recent platinum‑based regimen, with 39% on both arms with an interval of 6 to 12 months since the penultimate platinum regimen. Twenty-four percent of those treated with ZEJULA and 26% treated with placebo had received prior bevacizumab therapy. Approximately 50% of patients had 3 or more lines of treatment.

The trial demonstrated a statistically significant improvement in PFS for patients randomized to ZEJULA as compared with placebo in the gBRCAmut cohort (Table 11 and Figure 2).

Table 11. Efficacy Results – NOVA gBRCAmut Cohort (IRC Assessmenta)
 | ZEJULA; (n = 138) | Placebo; (n = 65)
Progression-free survival median in months (95% CI) | 21.0; (12.9, NR) | 5.5; (3.8, 7.2)
Hazard ratiob (95% CI) | 0.26; (0.17, 0.41)
P valuec | <0.0001
gBRCAmut = germline BRCA-mutated; IRC = Independent Review Committee; NR = Not Reached.
a Efficacy analysis was based on blinded central independent radiologic and clinical oncology review committee.
b Based on a stratified Cox proportional hazards model.
c Based on a stratified log-rank test.

Figure 2. Progression-Free Survival – NOVA gBRCAmut Cohort Based on IRC Assessment (N = 203)

gBRCAmut = germline BRCA-mutated; IRC = Independent Review Committee.

A final OS analysis was conducted after 154 events were observed. Exploratory OS results showed a HR of 0.85 (95% CI: 0.61, 1.20) in the gBRCAmut cohort with a median OS of 40.9 months (95% CI: 34.9, 52.9) for patients treated with ZEJULA and 38.1 months (95% CI: 27.6, 47.3) for patients on placebo.

16 HOW SUPPLIED/STORAGE AND HANDLING

ZEJULA is available as oval-shaped, film-coated tablets containing 100 mg, 200 mg, or 300 mg of niraparib free base.

ZEJULA 100-mg tablets are gray, debossed with “100” on one side and “Zejula” on the other side. Bottle of 30 tablets (NDC 0173-0909-13).

ZEJULA 200-mg tablets are blue, debossed with “200” on one side and “Zejula” on the other side. Bottle of 30 tablets (NDC 0173-0912-13).

ZEJULA 300-mg tablets are green, debossed with “300” on one side and “Zejula” on the other side. Bottle of 30 tablets (NDC 0173-0915-13).

Store and dispense in the original bottle. Store at 20°C to 25°C (68°F to 77°F); excursions are permitted between 15°C to 30°C (59°F to 86°F) [see USP Controlled Room Temperature].

17 PATIENT COUNSELING INFORMATION

Advise the patient to read the FDA-approved patient labeling (Patient Information).

Myelodysplastic Syndrome/Acute Myeloid Leukemia

Advise patients to contact their healthcare provider if they experience weakness, feeling tired, fever, weight loss, frequent infections, bruising, bleeding easily, breathlessness, blood in urine or stool, and/or laboratory findings of low blood cell counts or a need for blood transfusions. This may be a sign of hematological toxicity or MDS or AML, which has been reported in patients treated with ZEJULA [see Warnings and Precautions (5.1)].

Bone Marrow Suppression

Advise patients that periodic monitoring of their blood counts is required. Advise patients to contact their healthcare provider for new onset of bleeding, fever, or symptoms of infection [see Warnings and Precautions (5.2)].

Hypertension and Cardiovascular Effects

Advise patients to undergo blood pressure and heart rate monitoring at least weekly for the first 2 months, then monthly for the first year of treatment and periodically thereafter. Advise patients to contact their healthcare provider if blood pressure is elevated [see Warnings and Precautions (5.3)].

Posterior Reversible Encephalopathy Syndrome

Inform patients that they are at risk of developing posterior reversible encephalopathy syndrome (PRES) that can present with signs and symptoms including seizure, headaches, altered mental status, or vision changes. Advise patients to contact their healthcare provider if they develop any of these signs or symptoms [see Warnings and Precautions (5.4)].

Dosing Instructions

Inform patients on how to take ZEJULA [see Dosage and Administration (2.2)]. ZEJULA should be taken once daily. Instruct patients that if they miss a dose of ZEJULA not to take an extra dose to make up for the one that they missed. They should take their next dose at the regularly scheduled time. Each tablet should be swallowed whole. ZEJULA may be taken with or without food. Bedtime administration may be a potential method for managing nausea.

Embryo-Fetal Toxicity

Advise females to inform their healthcare provider if they are pregnant or become pregnant. Inform female patients of the risk to a fetus and potential loss of the pregnancy [see Warnings and Precautions (5.5), Use in Specific Populations (8.1)].

Contraception

Advise females of reproductive potential to use effective contraception during treatment with ZEJULA and for 6 months after receiving the last dose [see Use in Specific Populations (8.3)].

Lactation

Advise patients not to breastfeed while taking ZEJULA and for 1 month after the last dose [see Use in Specific Populations (8.2)].

Trademarks are owned by or licensed to the GSK group of companies. Opadry is a trademark owned by or licensed to its respective owner and is not owned by or licensed to the GSK group of companies. The maker of Opadry is not affiliated with and does not endorse the GSK group of companies or its products.

Manufactured for

GlaxoSmithKline

Durham, NC 27701

©2025 GSK group of companies or its licensor.

ZJT:4PI

PATIENT INFORMATION

ZEJULA (zuh-JOO-luh)

(niraparib)

tablets

What is the most important information I should know about ZEJULA?

ZEJULA may cause serious side effects including:

- Bone marrow problems called myelodysplastic syndrome (MDS) or a type of cancer of the blood called acute myeloid leukemia (AML). Some people who have ovarian cancer and who have received previous treatment with chemotherapy or certain other medicines for their cancer have developed MDS or AML during treatment with ZEJULA. MDS or AML may lead to death. If you develop MDS or AML, your healthcare provider will stop treatment with ZEJULA.
Symptoms of low blood cell counts (low red blood cells, low white blood cells, and low platelets) are common during treatment with ZEJULA, but can be a sign of serious bone marrow problems, including MDS or AML. Symptoms may include:

- weakness
- feeling tired
- weight loss
- frequent infections

- fever
- shortness of breath
- blood in urine or stool
- bruising or bleeding more easily

Your healthcare provider will do blood tests to check your blood cell counts:
  1. before treatment with ZEJULA.
  2. weekly for the first month of treatment with ZEJULA.
  3. every month for the next 11 months, then as needed during treatment with ZEJULA.
2. High blood pressure. High blood pressure is common during treatment with ZEJULA and can become serious. Your healthcare provider will check your blood pressure and heart rate at least weekly for the first 2 months, then monthly for the first year and as needed thereafter during your treatment with ZEJULA.
3. Posterior reversible encephalopathy syndrome (PRES). PRES is a condition that affects the brain and may happen during treatment with ZEJULA. If you have headache, vision changes, confusion, or seizure with or without high blood pressure, please contact your healthcare provider.

See “What are the possible side effects of ZEJULA?” for more information about side effects.

What is ZEJULA?

ZEJULA is a prescription medicine used to treat adults for:

- maintenance treatment of advanced ovarian cancer, fallopian tube cancer, or primary peritoneal cancer with a certain type of abnormal BRCA gene or a positive laboratory tumor test for genomic instability called homologous recombination deficiency (HRD). ZEJULA is used after the cancer has responded (complete or partial response) to treatment with first-line platinum-based chemotherapy.
- maintenance treatment of ovarian cancer, fallopian tube cancer, or primary peritoneal cancer with a certain type of inherited (germline) abnormal BRCA gene that comes back. ZEJULA is used after the cancer has responded (complete or partial response) to treatment with platinum-based chemotherapy. Your healthcare provider will perform a test to make sure that ZEJULA is right for you.

It is not known if ZEJULA is safe and effective in children.

Before taking ZEJULA, tell your healthcare provider about all of your medical conditions, including if you:

- have heart problems.
- have liver problems.
- have high blood pressure.
- are pregnant or plan to become pregnant. ZEJULA can harm your unborn baby and may cause loss of pregnancy (miscarriage).
  - If you are able to become pregnant, your healthcare provider should perform a pregnancy test before you start treatment with ZEJULA.
  - Females who are able to become pregnant should use effective birth control (contraception) during treatment with ZEJULA and for 6 months after the last dose of ZEJULA. Talk to your healthcare provider about birth control methods that may be right for you.
  - Tell your healthcare provider right away if you become pregnant.
- are breastfeeding or plan to breastfeed. It is not known if ZEJULA passes into your breast milk. Do not breastfeed during treatment with ZEJULA and for 1 month after the last dose of ZEJULA. Talk to your healthcare provider about the best way to feed your baby during this time.

Tell your healthcare provider about all the medicines you take, including prescription and over-the-counter medicines, vitamins, and herbal supplements.

How should I take ZEJULA?

- Take ZEJULA exactly as your healthcare provider tells you to.
- Take ZEJULA 1 time each day, at the same time each day.
- ZEJULA may be taken with or without food.
- ZEJULA tablets should be swallowed whole. Do not chew, crush, or split ZEJULA tablets before swallowing.
- Taking ZEJULA at bedtime may help relieve any nausea symptoms you may have.
- Do not stop taking ZEJULA without first talking with your healthcare provider.
- If you miss a dose of ZEJULA, take your next dose at your scheduled time. Do not take an extra dose to make up for a missed dose.
- If you vomit after taking a dose of ZEJULA, do not take an extra dose. Take your next dose at your scheduled time.
- If you take too much ZEJULA, call your healthcare provider or go to the nearest hospital emergency room right away.

What are the possible side effects of ZEJULA?

ZEJULA may cause serious side effects, including:

- See “What is the most important information I should know about ZEJULA?”

The most common side effects of ZEJULA include:

- nausea
- tiredness
- constipation
- pain in your muscles and back
- pain in the stomach area
- vomiting
- loss of appetite
- trouble sleeping
- headache

- shortness of breath
- rash
- diarrhea
- cough
- dizziness
- changes in the amount or color of your urine
- urinary tract infection
- low levels of magnesium in the blood

Your healthcare provider may change your dose, temporarily stop treatment, or permanently stop treatment with ZEJULA if you have certain side effects.

These are not all the possible side effects of ZEJULA.

Call your doctor for medical advice about side effects. You may report side effects to FDA at 1-800-FDA-1088.

How should I store ZEJULA?

- Store ZEJULA at room temperature between 68°F to 77°F (20°C to 25°C).
- Store ZEJULA tablets in the original bottle.

Keep ZEJULA and all medicines out of the reach of children.

General information about the safe and effective use of ZEJULA.

Medicines are sometimes prescribed for purposes other than those listed in a Patient Information leaflet. Do not use ZEJULA for a condition for which it was not prescribed. Do not give ZEJULA to other people, even if they have the same symptoms that you have. It may harm them. You can ask your healthcare provider or pharmacist for information about ZEJULA that is written for health professionals.

What are the ingredients in ZEJULA?

Active ingredient: niraparib.

Inactive ingredients:

Core tablet: crospovidone, lactose monohydrate, magnesium stearate, microcrystalline cellulose, povidone, and silicon dioxide.

Film-coating: Opadry II Gray (100 mg), Opadry II Blue (200 mg), or Opadry II Green (300 mg).

For more information about ZEJULA, call 1-888-825-5249.

Trademarks are owned by or licensed to the GSK group of companies. Opadry is a trademark owned by or licensed to its respective owner and is not owned by or licensed to the GSK group of companies. The maker of Opadry is not affiliated with and does not endorse the GSK group of companies or its products.

Manufactured for:

GlaxoSmithKline, Durham, NC 27701

©2025 GSK group of companies or its licensor.

ZJT:2PIL

This Patient Information has been approved by the U.S. Food and Drug Administration Revised: June/2025

PACKAGE LABEL

PRINCIPAL DISPLAY PANEL

NDC 0173-0909-13

Zejula

(niraparib)

tablets

100 mg

GSK

Rx only

30 tablets

Each 100-mg tablet is equivalent to 159.3 mg of niraparib tosylate monohydrate.

Store at 20°C to 25°C (68°F to 77°F); excursions are permitted between 15°C to 30°C (59°F to 86°F).[See USP Controlled Room Temperature]. Store and dispense in the original bottle.

Do not accept if membrane seal under cap is missing or broken. See prescribing information for dosage information. Keep out of reach of children.

Trademarks owned or licensed by GSK.

Mfd for GSK, Durham, NC 27701

©20243 GSK or licensor.

Rev. 9/24

MCK-150667-01

PACKAGE LABEL

PRINCIPAL DISPLAY PANEL

NDC 0173-0912-13

Zejula

(niraparib)

tablets

200 mg

GSK

Rx only

30 tablets

Each 200-mg tablet is equivalent to 318.7 mg of niraparib tosylate monohydrate.

Store at 20°C to 25°C (68°F to 77°F); excursions are permitted between 15°C to 30°C (59°F to 86°F).[See USP Controlled Room Temperature]. Store and dispense in the original bottle.

Do not accept if membrane seal under cap is missing or broken. See prescribing information for dosage information. Keep out of reach of children.

Trademarks owned or licensed by GSK.

Mfd for GSK, Durham, NC 27701

©2024 GSK or licensor.

Rev. 9/24

MCK-150668-01

PACKAGE LABEL

PRINCIPAL DISPLAY PANEL

NDC 0173-0915-13

Zejula

(niraparib)

tablets

300 mg

GSK

Rx only

30 tablets

Each 300-mg tablet is equivalent to 478.0 mg of niraparib tosylate monohydrate.

Store at 20°C to 25°C (68°F to 77°F); excursions are permitted between 15°C to 30°C (59°F to 86°F).[See USP Controlled Room Temperature]. Store and dispense in the original bottle.

Do not accept if membrane seal under cap is missing or broken. See prescribing information for dosage information. Keep out of reach of children.

Trademarks owned or licensed by GSK.

Mfd for GSK, Durham, NC 27701

©2024 GSK or licensor.

Rev. 9/24

MCK-150670-01